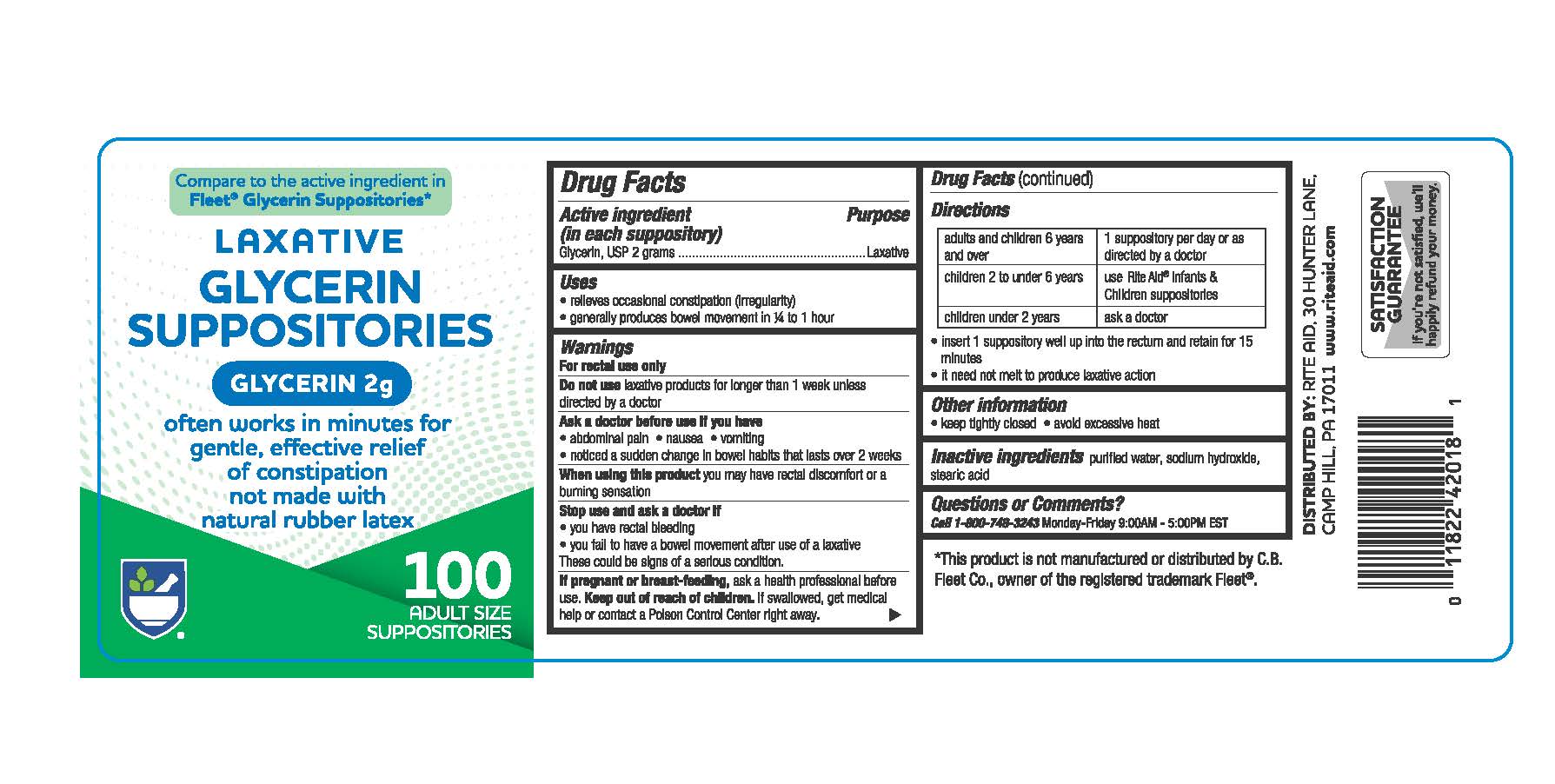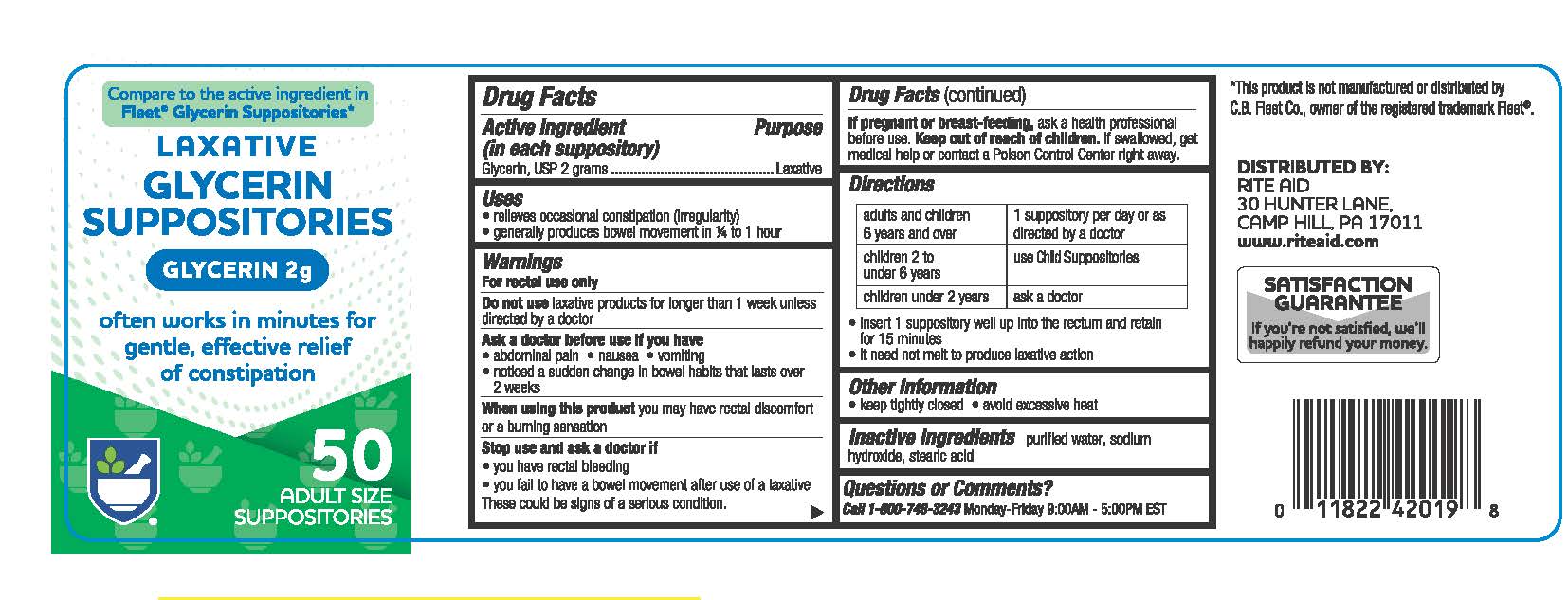 DRUG LABEL: Rite-Aid Glycerin
NDC: 11822-9100 | Form: SUPPOSITORY
Manufacturer: RITE AID CORPORATION
Category: otc | Type: HUMAN OTC DRUG LABEL
Date: 20260114

ACTIVE INGREDIENTS: GLYCERIN 2 g/1 1
INACTIVE INGREDIENTS: STEARIC ACID; SODIUM HYDROXIDE; WATER

Rite-Aid®Glycerin Suppositories

Active Ingredient

Active Ingredient (in each suppository) Purpose
Glycerin, USP 2 grams ............................................Laxative

Uses

Uses- relieves occasional constipation (irregularity)

- generally produces bowel movement in 1/4 to 1 hour

Warnings

For rectal use only

Do not use laxative products for longer than 1 week unless directed by a doctor

Ask a doctor before use if you have

- stomach pain - nausea - vomiting - noticed a sudden change in bowel habits that lasts over 2 weeks

When using this product you may have rectal discomfort or a burning sensation

Stop use and ask a doctor if you have rectal bleeding or fail to have a bowel movement after use of a laxative. These could be signs of a serious condition.

If pregnant or breast-feeding, ask a health professional before use.

Keep out of reach of children. If swallowed, get medical help or contact a Poison Control Center right away.

Directions

adults and children 6 years and over Insert 1 suppository well into the rectum and retain for 15 minutes; it need not melt to

produce laxative action. Do not exceed 1 suppository daily or as directed by a doctor

children 2 to under 6 years use Child Suppositories
children under 2 years ask a doctor

Other information

- keep tightly closed - avoid excessive heat

Inactive ingredients

purified water, sodium hydroxide, stearic acid